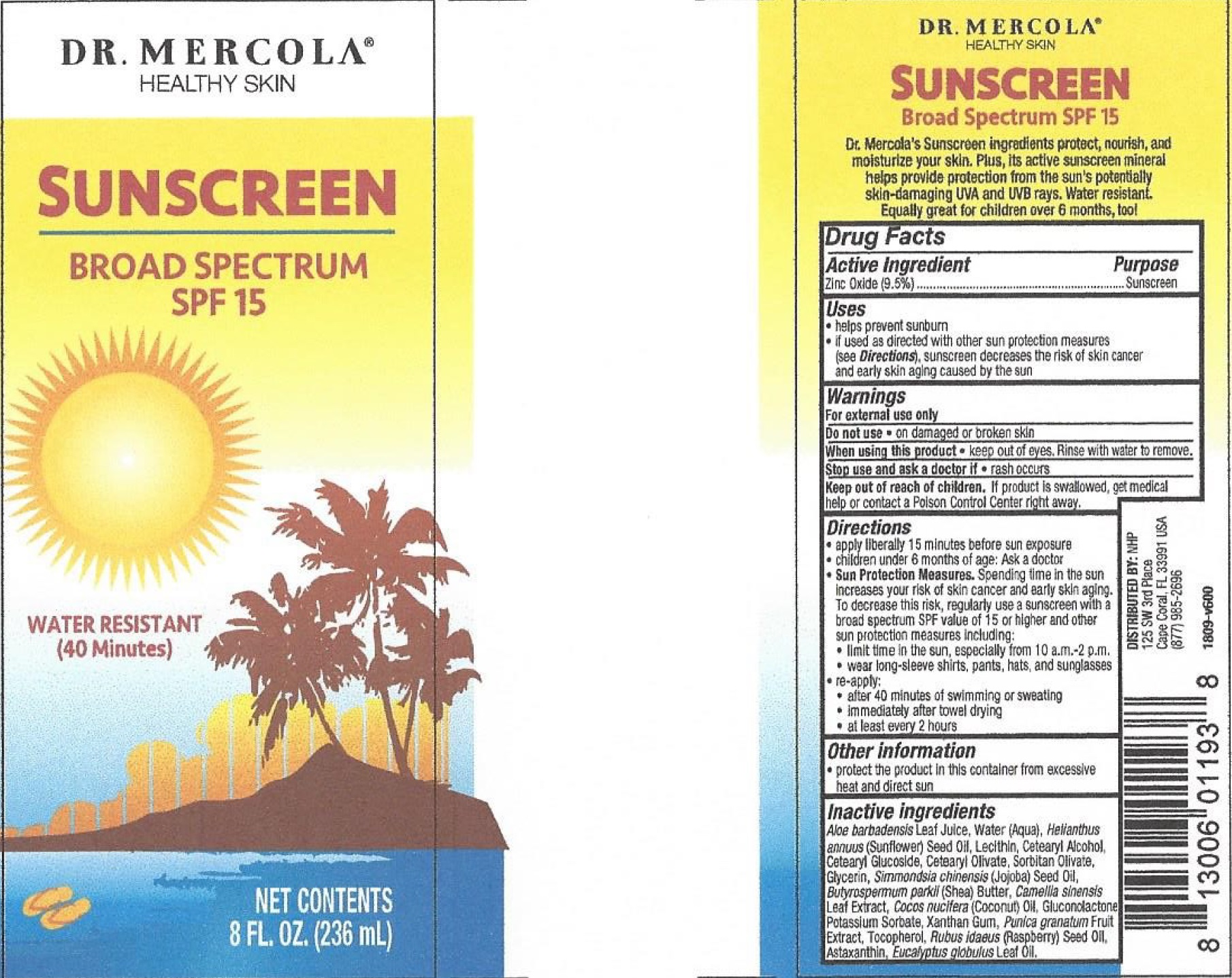 DRUG LABEL: Dr Mercola Broad Spectrum SPF15
NDC: 71239-788 | Form: CREAM
Manufacturer: Natural Health Partners, LLC
Category: otc | Type: HUMAN OTC DRUG LABEL
Date: 20250528

ACTIVE INGREDIENTS: ZINC OXIDE 95 mg/1 mL
INACTIVE INGREDIENTS: ALOE VERA LEAF; WATER; HELIANTHUS ANNUUS FLOWERING TOP; CETOSTEARYL ALCOHOL; CETEARYL GLUCOSIDE; CETEARYL OLIVATE; SORBITAN OLIVATE; GLYCERIN; JOJOBA OIL; SHEA BUTTER; GREEN TEA LEAF; COCONUT OIL; GLUCONOLACTONE; POTASSIUM SORBATE; XANTHAN GUM; POMEGRANATE; TOCOPHEROL; RASPBERRY SEED OIL; ASTAXANTHIN; EUCALYPTUS OIL

Dr. Mercola Broad Spectrum SPF-15 Cream

Active Ingredient

Zinc Oxide (9.5%)

Purpose

Sunscreen

Uses

- helps prevent sunburn
- if used as directed with other sun protection measures (see), sunscreen decreases the risk of skin cancer and early skin aging caused by the sun Directions

Warnings

For external use only

Do not use

- on damaged or broken skin

When using this product

- keep out of eyes. Rinse with water to remove.

Stop use and ask a doctor if

- rash occurs

Keep out of reach of children.

If product is swallowed, get medical help or contact a Poison Control Center right away.

Directions

- apply liberally 15 minutes before sun exposure
- children under 6 months of age: Ask a doctor
- Spending time in the sun increases yours risk of skin cancer and early skin aging. To decrease this risk, regularly use a sunscreen with a broad spectrum SPF value of 15 or higher and other sun protection measures including: Sun Protection Measures.
- limit time in the sun, especially from 10 a.m. -2 p.m.
- wear long-sleeve shirts, pants, hats and sunglasses
- re-apply:
- after 40 minutes of swimming or sweating
- immediately after towel drying
- at least every 2 hours

Other information

- protect the product in this container from excessive heat and direct sun

Inactive ingredients

Aloe barbadensis Leaf Juice, Water (Aqua), Helianthus annuus (Sunflower) Seed Oil, Lecithin, Cetearyl Alcohol, Cetearyl Glucoside, Cetearyl Olivate, Sorbitan Olivate, Glycerin, Simmondsia chinensis (Jojoba) Seed Oil, Butyrospermum parkii (Shea) Butter, Camellia sinensis Leaf Extract, Cocos nucifera (Coconut) Oil, Gluconolatone Potassium Sorbate, Xanthan Gum, Punica granatum Fruit Extract, Tocopherol, Rubus idaeus (Raspberry) Seed Oil, Astaxanthin, Eucalyptus globulus Leaf Oil.